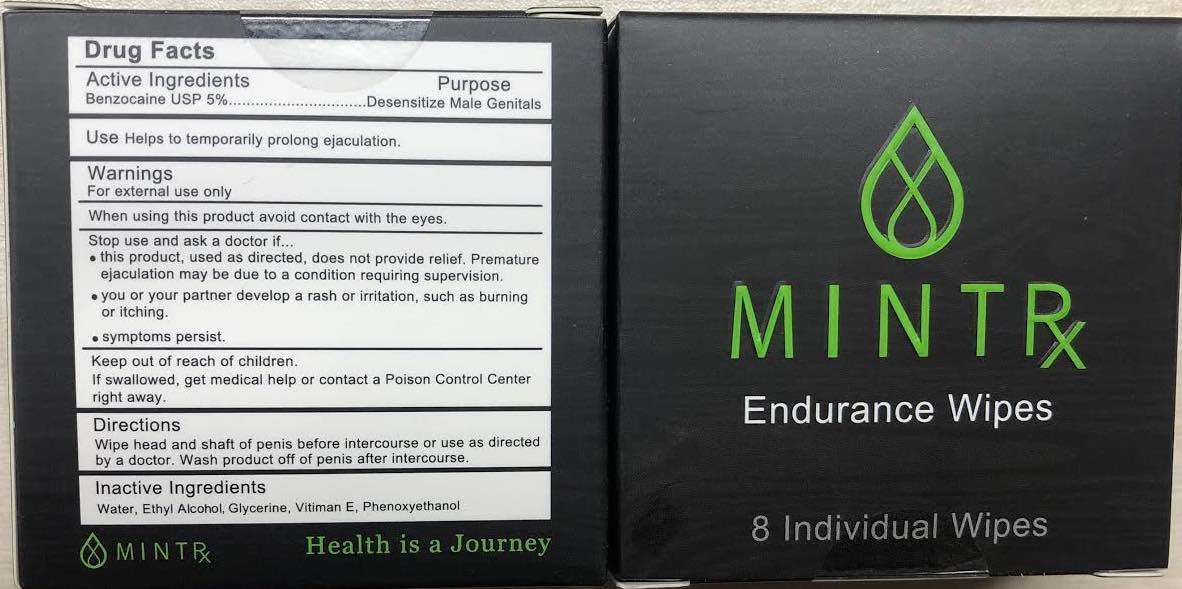 DRUG LABEL: MINT RX ENDURANCE WIPES
NDC: 77691-433 | Form: LIQUID
Manufacturer: PHARMAMEDRX
Category: otc | Type: HUMAN OTC DRUG LABEL
Date: 20200520

ACTIVE INGREDIENTS: BENZOCAINE 5 g/100 mL
INACTIVE INGREDIENTS: WATER; ALCOHOL; GLYCERIN; TOCOPHEROL; PHENOXYETHANOL

MINT RX ENDURANCE WIPES
BENZOCAINE USP 5%

Active ingredient

Benzocaine 5%

Purpose

Male genital desensitizer

Keep out of reach of children

If swallowed, get medical help or contact a poison control center right away

Use

Helps in temporarily prolonging time until ejaculation

Warnings

For external use ony

When using this product avoid contact with eyes

Stop use and ask a doctor if

This product, used as directed, does not provide relief. Premature ejaculation may be due to a condition requiring medical supervision

You or your partner develop a rash or irritation such as burning or itching

Symptoms persist

Directions

Wipe head and shaft of penis before intercourse or use as directed by a doctor. Wash product off of penis after intercourse

Inactive ingredients

Purified water, ethyl alcohol, glycerin, Vitamin E, phenoxyethanol